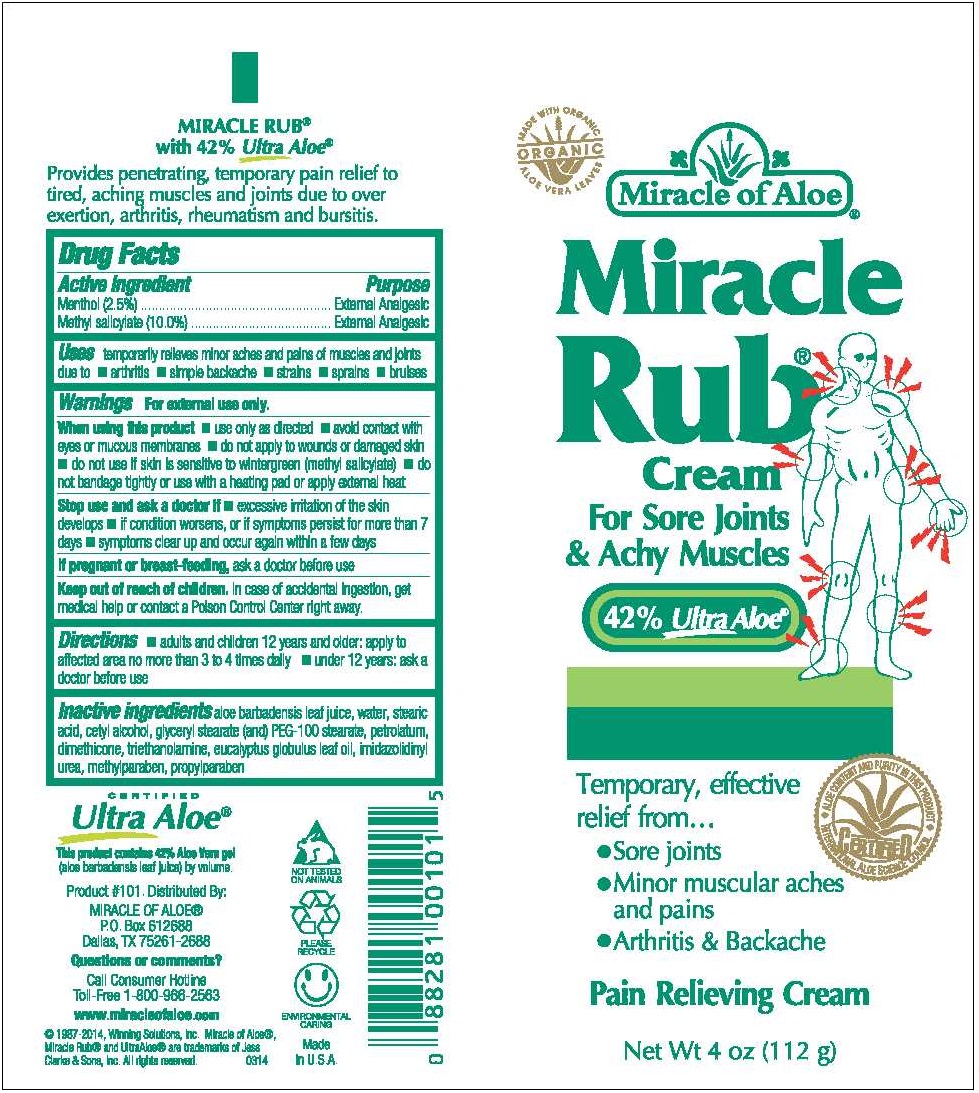 DRUG LABEL: Miracle Rub
NDC: 66391-1603 | Form: CREAM
Manufacturer: Winning Solutions
Category: otc | Type: HUMAN OTC DRUG LABEL
Date: 20230112

ACTIVE INGREDIENTS: MENTHOL 2.5 g/106 g; METHYL SALICYLATE 10 g/106 g
INACTIVE INGREDIENTS: ALOE VERA LEAF; WATER; STEARIC ACID; CETYL ALCOHOL; GLYCERYL STEARATE SE; PEG-100 STEARATE; PETROLATUM; DIMETHICONE; TROLAMINE; EUCALYPTUS OIL; IMIDUREA; METHYLPARABEN; PROPYLPARABEN; MANGO

WINNING SOLUTIONS - MIRACLE RUB (66391-1603)

Active Ingredient : Menthol 2.5%

Methylsalieylate 10.0%

Purpose : External Analgesic

Warnings: For external use only .

Keep out of reach of children : In case of accidental ingestion, get medical help or contact a Poison Control center right away.

DOSAGE AND ADMINISTRATION

Directions : adults and children 12 years and older apply to affected area no more than 3 to 4 times daily

under 12 years ask a doctor before use

INDICATIONS AND USAGE

Uses: Temporarly relieves minor aches and pains of muscles and joints due to

- arthritis
- simple backache
- strains
- sprains
- bruises

INACTIVE INGREDIENT

aloe barabardensis leaf Juice, water, stearic acid, cetyl alcohol, glyceryl stearate, PEG-100 stearte, petrolatum, dimethicone, triethanolamine, eucalyptus globulus leaf oil, imidazolidinyl urea, methylparaben, propylparaben